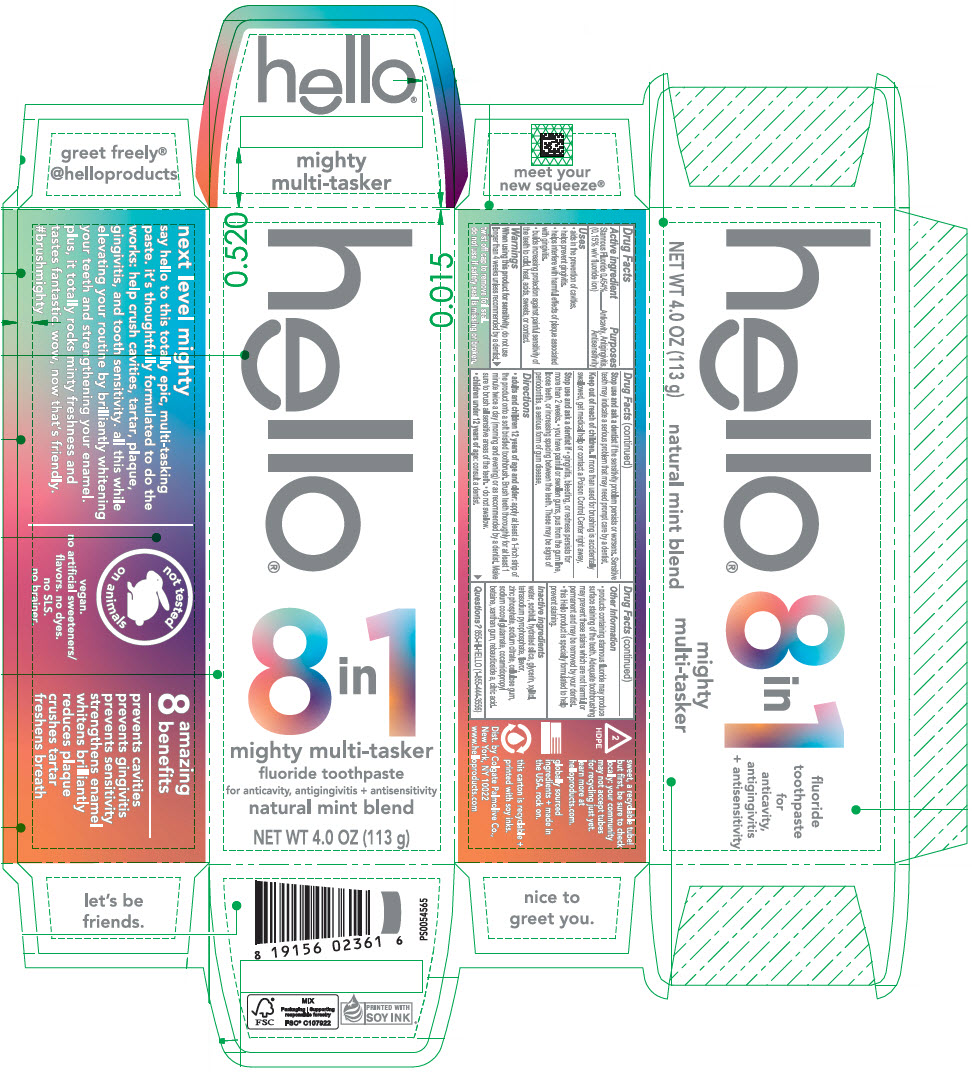 DRUG LABEL: Hello Mighty Multi tasker
NDC: 35000-681 | Form: PASTE, DENTIFRICE
Manufacturer: Colgate-Palmolive Company
Category: otc | Type: HUMAN OTC DRUG LABEL
Date: 20250415

ACTIVE INGREDIENTS: STANNOUS FLUORIDE 1.1 mg/1 g
INACTIVE INGREDIENTS: WATER; SORBITOL; HYDRATED SILICA; GLYCERIN; XYLITOL; SODIUM PYROPHOSPHATE; ZINC PHOSPHATE; SODIUM CITRATE, UNSPECIFIED FORM; CARBOXYMETHYLCELLULOSE SODIUM, UNSPECIFIED; SODIUM COCOYL GLUTAMATE; COCAMIDOPROPYL BETAINE; XANTHAN GUM; STEVIA REBAUDIUNA LEAF; ANHYDROUS CITRIC ACID

Hello® Mighty Multi tasker

Drug Facts

Active ingredient

Stannous Fluoride 0.454% (0.15% w/v fluoride ion)

Purposes

Anticavity, Antigingivitis, Antisensitivity

Uses

- aids in the prevention of cavities.
- helps prevent gingivitis.
- helps interfere with harmful effects of plaque associated with gingivitis.
- builds increasing protection against painful sensitivity of the teeth to cold, heat, acids, sweets, or contact.

Warnings

When using this product for sensitivity, do not use longer than 4 weeks unless recommended by a dentist.

Stop use and ask a dentist if the sensitivity problem persists or worsens. Sensitive teeth may indicate a serious problem that may need prompt care by a dentist.

Keep out of reach of children. If more than used for brushing is accidentally swallowed, get medical help or contact a Poison Control Center right away.

Stop use and ask a dentist if

- gingivitis, bleeding, or redness persists for more than 2 weeks.
- you have painful or swollen gums, pus from the gum line, loose teeth, or increasing spacing between the teeth. These may be signs of periodontitis, a serious form of gum disease.

Directions

- adults and children 12 years of age and older: apply at least a 1-inch strip of the product onto a soft bristled toothbrush. Brush teeth thoroughly for at least 1 minute twice a day (morning and evening) or as recommended by a dentist. Make sure to brush all sensitive areas of the teeth.
- do not swallow.
- children under 12 years of age: consult a dentist.

Other Information

- products containing stannous fluoride may produce surface staining of the teeth. Adequate toothbrushing may prevent these stains which are not harmful or permanent and may be removed by your dentist.
- this Hello product is specially formulated to help prevent staining.

Inactive ingredients

water, sorbitol, hydrated silica, glycerin, xylitol, tetrasodium pyrophosphate, flavor, zinc phosphate, sodium citrate, cellulose gum, sodium cocoyl glutamate, cocamidopropyl betaine, xanthan gum, rebaudioside a, citric acid.

Questions?

855-HI-HELLO (1-855-444-3556)

Dist. by Colgate-Palmolive Co.
New York, NY 10022

PRINCIPAL DISPLAY PANEL - 113 g Tube Carton

hello®

8 in 1

mighty multi-tasker
fluoride toothpaste
for anticavity, antigingivitis + antisensitivity
natural mint blend

NET WT 4.0 OZ (113 g)